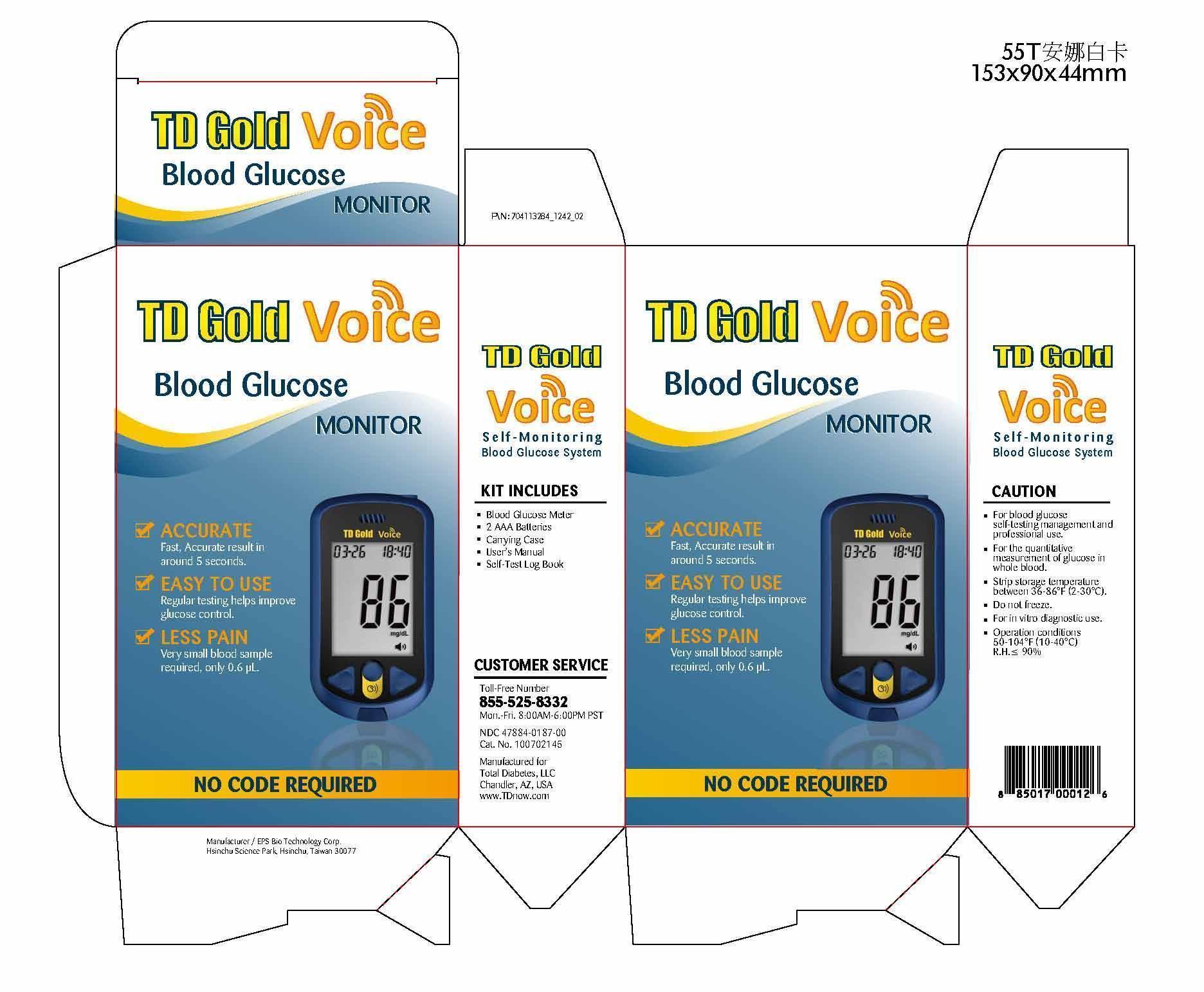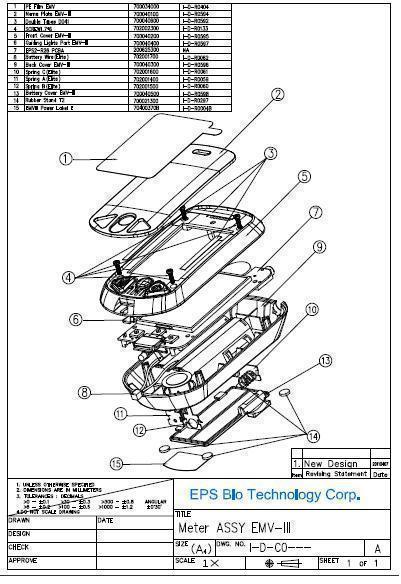 DRUG LABEL: TD Gold Voice Blood Glucose Monitor Set
NDC: 47884-187
Manufacturer: EPS Bio Technology Corp.
Category: other | Type: MEDICAL DEVICE
Date: 20131022

Home Use Medical Device : TD Gold Voice Self-monitoing Blood Glucose System